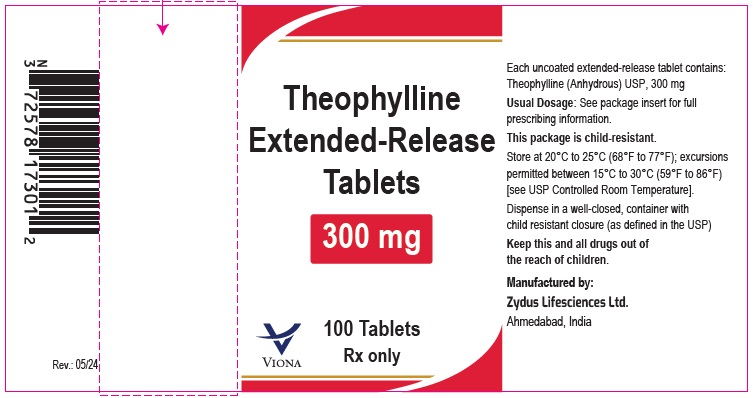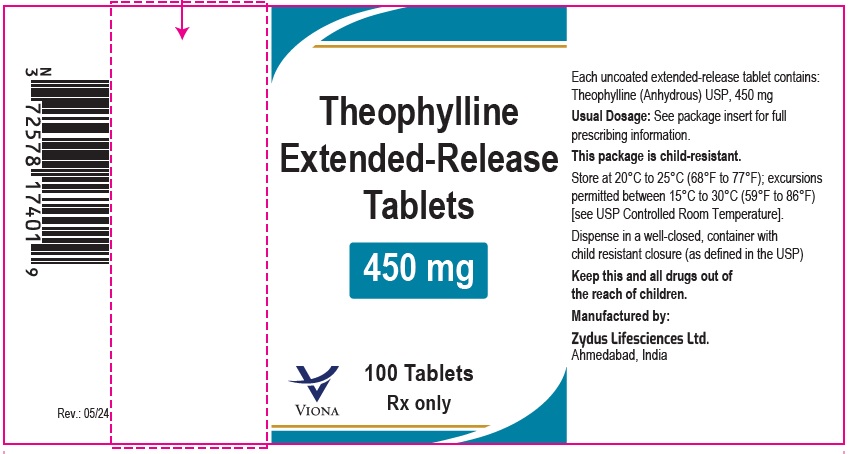 DRUG LABEL: Theophylline
NDC: 70771-1782 | Form: TABLET, EXTENDED RELEASE
Manufacturer: Zydus Lifesciences Limited
Category: prescription | Type: HUMAN PRESCRIPTION DRUG LABEL
Date: 20240522

ACTIVE INGREDIENTS: THEOPHYLLINE ANHYDROUS 300 mg/1 1
INACTIVE INGREDIENTS: HYPROMELLOSE 2208 (100 MPA.S); LACTOSE MONOHYDRATE; MAGNESIUM STEARATE; POVIDONE

Theophylline Extended-Release Tablets

PACKAGE LABEL.PRINCIPAL DISPLAY PANEL

Theophylline extended-release tablets, 300 mg

100 Tablets

NDC 70771-1782-1

Rx only

Theophylline extended-release tablets, 450 mg

100 Tablets

NDC 70771-1783-1

Rx only